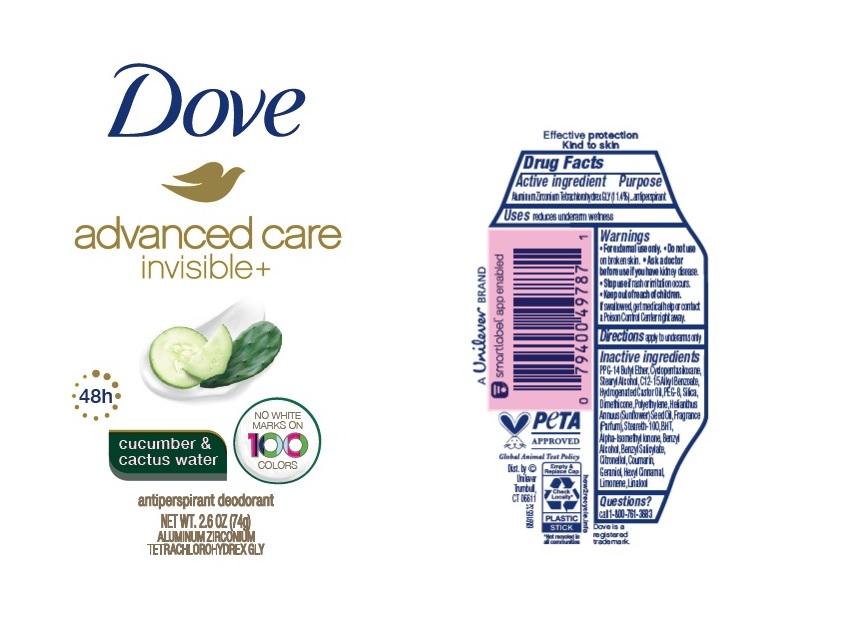 DRUG LABEL: Dove
NDC: 64942-2052 | Form: STICK
Manufacturer: Conopco Inc. d/b/a/ Unilever
Category: otc | Type: HUMAN OTC DRUG LABEL
Date: 20241106

ACTIVE INGREDIENTS: ALUMINUM ZIRCONIUM TETRACHLOROHYDREX GLY 11.4 g/100 g
INACTIVE INGREDIENTS: BENZYL SALICYLATE; LINALOOL, (+/-)-; GERANIOL; ISOMETHYL-.ALPHA.-IONONE; HIGH DENSITY POLYETHYLENE; CYCLOMETHICONE 5; HYDROGENATED CASTOR OIL; BUTYLATED HYDROXYTOLUENE; PPG-14 BUTYL ETHER; STEARYL ALCOHOL; SUNFLOWER OIL; SILICON DIOXIDE; ALKYL (C12-15) BENZOATE; DIMETHICONE; STEARETH-100; POLYETHYLENE GLYCOL 400; COUMARIN; BENZYL ALCOHOL; .BETA.-CITRONELLOL, (R)-; LIMONENE, (+)-; .ALPHA.-HEXYLCINNAMALDEHYDE

Dove Advanced Care Invisble Cucumber & Cactus Water 48h Antiperspirant Deodorant

Drug Facts

Active ingredient

Aluminum Zirconium Tetrachlorohydrex GLY (11.4 %)

Purpose

antiperspirant

Uses

• reduces underarm wetness

Warnings

• For external use only.
• Do not use on broken skin .
• Ask a doctor before use if you have kidney disease.
• Stop use if rash or irritation occurs.

• Keep out of reach of children.

If swallowed, get medical help or contact a Poison Control Center right away.

Directions

apply to underarms only

Inactive ingredients

PPG-14 Butyl Ether, Cyclopentasiloxane, Stearyl Alcohol, C12-15 Alkyl Benzoate, Hydrogenated Castor Oil, PEG-8, Silica, Dimethicone, Polyethylene, Helianthus Annuus (Sunflower) Seed Oil, Fragrance (Parfum), Steareth-100, BHT, Alpha-Isomethyl Ionone, Benzyl Alcohol, Benzyl Salicylate, Citronellol, Coumarin, Geraniol, Hexyl Cinnamal, Limonene, Linalool

Questions?

Call 1-800-761-3683